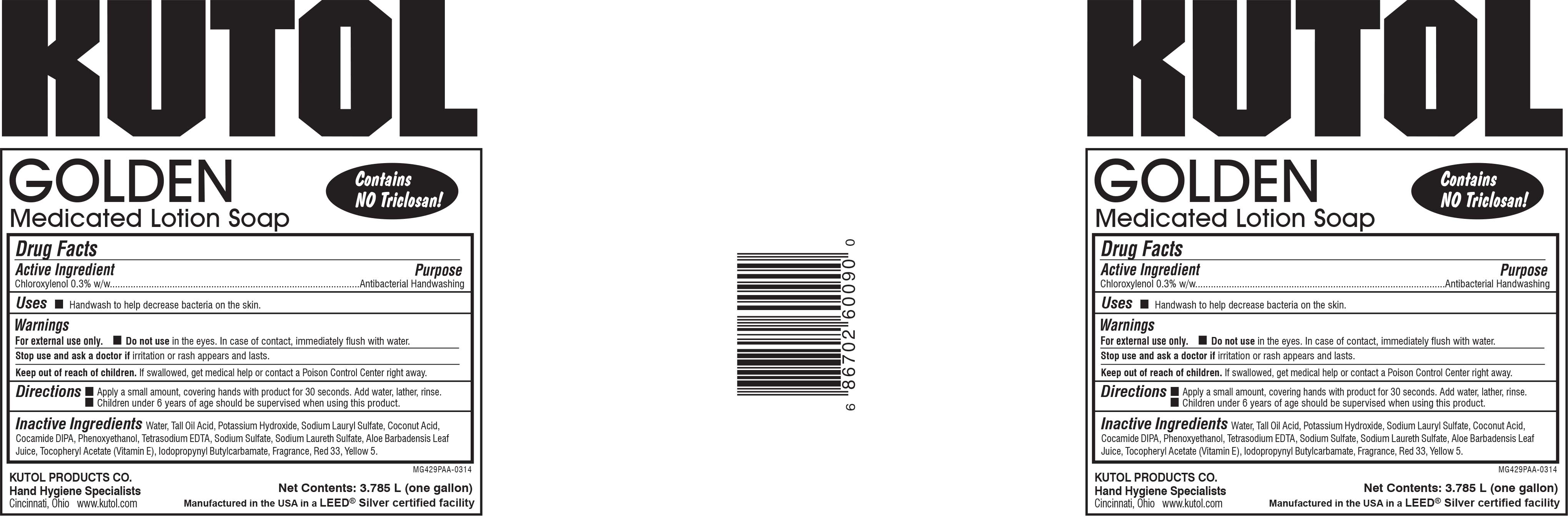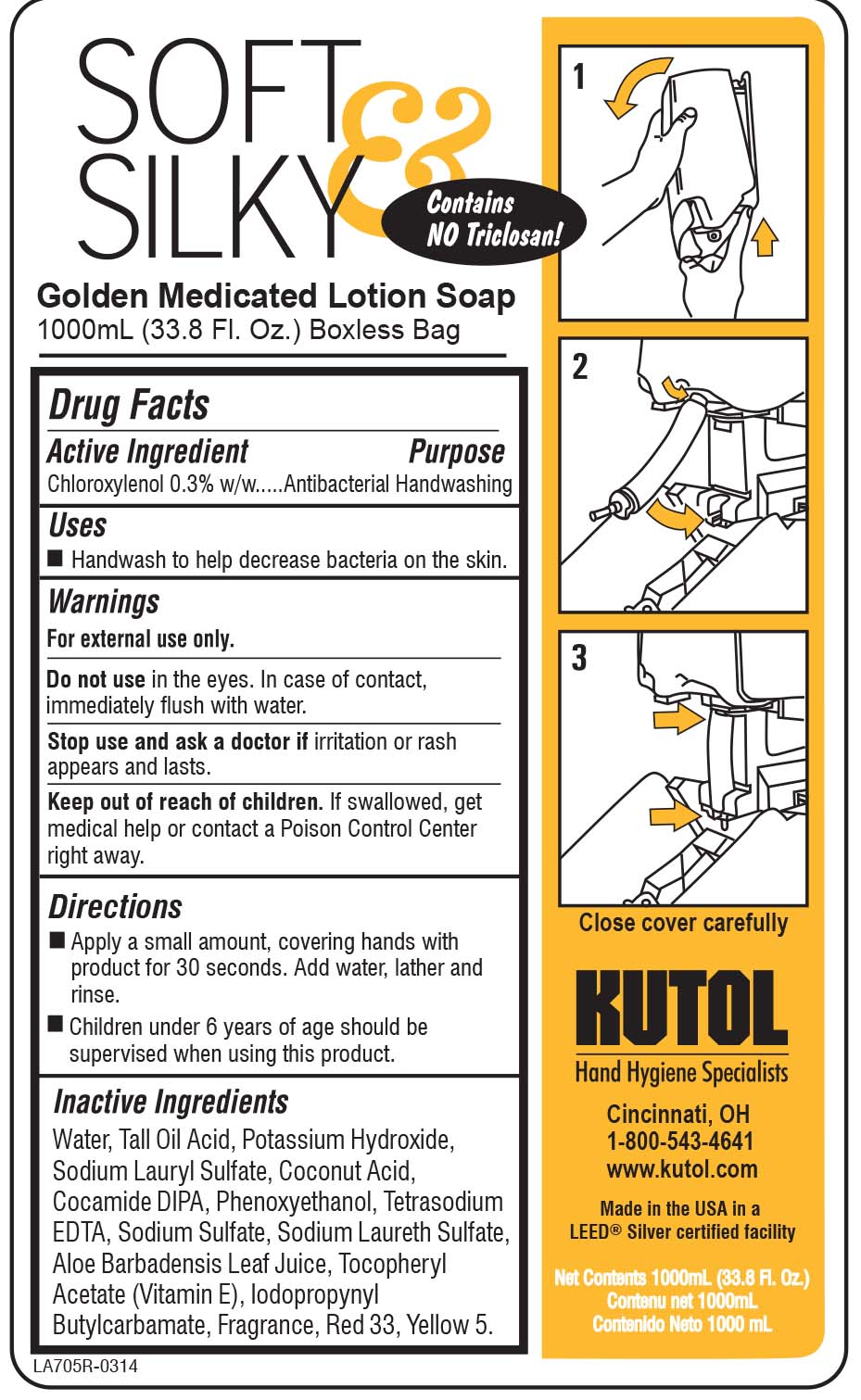 DRUG LABEL: Golden Medicated
NDC: 50865-060 | Form: SOLUTION
Manufacturer: Kutol Products Company
Category: otc | Type: HUMAN OTC DRUG LABEL
Date: 20241218

ACTIVE INGREDIENTS: CHLOROXYLENOL 0.3 g/100 mL
INACTIVE INGREDIENTS: WATER; POTASSIUM HYDROXIDE; COCONUT ACID; SODIUM LAURYL SULFATE; PHENOXYETHANOL; SODIUM LAURETH SULFATE; IODOPROPYNYL BUTYLCARBAMATE; SODIUM SULFATE; D&C RED NO. 33; FD&C YELLOW NO. 5; EDETATE SODIUM; TALL OIL ACID; ALOE VERA LEAF; .ALPHA.-TOCOPHEROL ACETATE; COCO DIISOPROPANOLAMIDE

Kutol F060

ACTIVE INGREDIENT

Chloroxylenol 0.3% w/w.......Antibacterial Handwashing

INACTIVE INGREDIENT

Water, Tall Oil Acid, Potassium Hydroxide, Sodium Lauryl Sulfate, Coconut Acid, Cocamide DIPA, Phenoxyethanol, Tetrasodium EDTA, Sodium Sulfate, Sodium Laureth Sulfate, Aloe Barbadensis Leaf Juice, Tocopheryl Acetate (Vitamin E), Iodopropynyl Butylcarbamate, Fragrance, Red 33, Yellow 5.

PURPOSE

Handwash to help decrease bacteria on the skin.

WARNINGS

For external use only.

Do not usein the eyes. In case of contact, immediately flush with water.

Stop use and ask a doctor ifirritation or rash appears and lasts.

Keep out of reach of children.If swallowed, get medical help or contact a Poison Control Center right away.

DOSAGE AND ADMINISTRATION

- Apply a small amount, covering hands with product for 30 seconds. Add water, lather and rinse.
- Children under 6 years of age should be supervised when using this product.

INDICATIONS AND USAGE

Handwash to help decrease bacteria on the skin.

Do not use in the eyes. In case of contact, immediately flush with water.

Stop use and ask a doctor if irritation or rash appears and lasts.

Keep out of reach of children. If swallowed, get medical help or contact a Poison Control Center right away.

Keep out of reach of children. If swallowed, get medical help or contact a Poison Control Center right away.

PACKAGE LABEL

50865-060-09.jpg

PACKAGE LABEL

50865-060-27.jpg